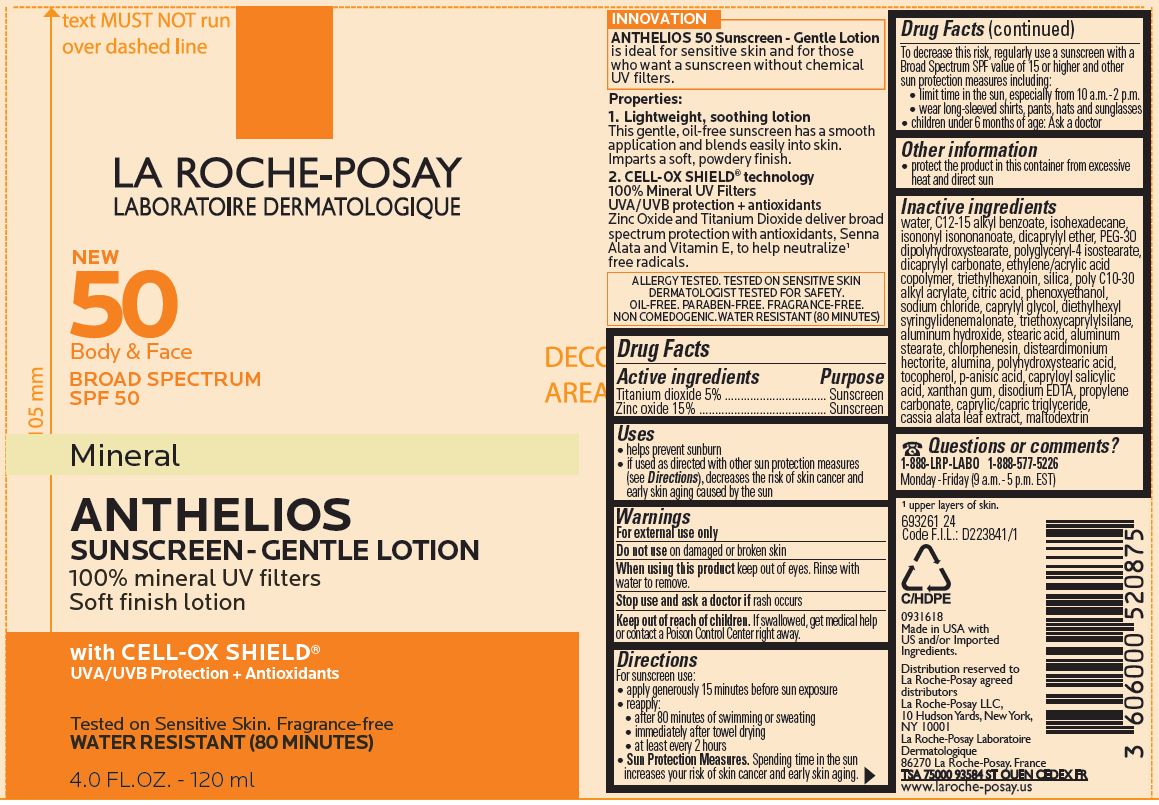 DRUG LABEL: La Roche Posay New 50 Body and Face SPF 50 Mineral Anthelios Gentle 100 percent mineral UV filters Soft finish with Cell Ox Shield
NDC: 49967-091 | Form: LOTION
Manufacturer: L'Oreal USA Products Inc
Category: otc | Type: HUMAN OTC DRUG LABEL
Date: 20240101

ACTIVE INGREDIENTS: TITANIUM DIOXIDE 50 mg/1 mL; ZINC OXIDE 150 mg/1 mL
INACTIVE INGREDIENTS: WATER; ALKYL (C12-15) BENZOATE; ISOHEXADECANE; ISONONYL ISONONANOATE; DICAPRYLYL ETHER; PEG-30 DIPOLYHYDROXYSTEARATE; POLYGLYCERYL-4 ISOSTEARATE; DICAPRYLYL CARBONATE; TRIETHYLHEXANOIN; SILICON DIOXIDE; CITRIC ACID MONOHYDRATE; PHENOXYETHANOL; SODIUM CHLORIDE; CAPRYLYL GLYCOL; DIETHYLHEXYL SYRINGYLIDENEMALONATE; TRIETHOXYCAPRYLYLSILANE; ALUMINUM HYDROXIDE; STEARIC ACID; ALUMINUM STEARATE; CHLORPHENESIN; DISTEARDIMONIUM HECTORITE; ALUMINUM OXIDE; TOCOPHEROL; P-ANISIC ACID; CAPRYLOYL SALICYLIC ACID; XANTHAN GUM; EDETATE DISODIUM; PROPYLENE CARBONATE; MEDIUM-CHAIN TRIGLYCERIDES; SENNA ALATA LEAF; MALTODEXTRIN

Drug Facts

Drug Facts

Titanium dioxide 5%

Zinc Oxide 15%

Purpose

Sunscreen

Uses

- helps prevent sunburn
- if used as directed with other sun protection measures (see Directions), decreases the risk of skin cancer and early skin aging cuased by the sun

Warnings

For external use only

Do not use

on damaged or broken skin

When using this product

keep out of eyes. Rinse with water to remove.

Stop use and ask a doctor if

rash occurs

Keep out of reach of children.

If swallowed, get medical help or contact a Poison Control Center right away.

Directions

For sunscreen use:

- apply generously 15 minutes before sun exposure
- reapply:
- after 80 minutes of swimming or sweating
- immediately after towel drying
- at least every 2 hours
- Sun Protection Measures. Spending time in the sun increases your risk of skin cancer and early skin aging. To decrease this risk, regularly use a sunscreen with a Broad Spectrum SPF value of 15 or higher and other sun protection measures including:
- limit time in the sun, especially from 10 a.m - 2 p.m.
- wear long-sleeved shirts, pants, hats and sunglasses
- children under 6 months of age: Ask a doctor

Other information

- protect the product is this container from excessive heat and direct sun

Inactive ingredients

water, C12-15 alkyl benzoate, isohexadecane, isononyl isononanoate, dicaprylyl ether, PEG-30 dipolyhydroxystearate, polyglyceryl-4 isostearate, dicaprylyl carbonate, ethylene/acrylic acid copolymer, triethylhexanoin, silica, poly C10-30 alkyl acrylate, citric acid, phenoxyethanol, sodium chloride, caprylyl glycol, diethylhexyl syringylidenemalonate, triethoxycaprylylsilane, aluminum hydroxide, stearic acid, aluminum stearate, chlorphnesin, disteardimonium hectorite, alumina, polyhydroxystearic acid, tocopherol, p-ansic acid, capryloyl salicylic acid, xanthan gum, disodium EDTA, propylene carbonate, caprylic/capric triglyceride, cassia alata leaf extract, maltodextrin

Questions or comments?

1-888-LRP-LABO 1-888-577-5226

Monday-Friday (9 a.m.-5 p.m. EST)